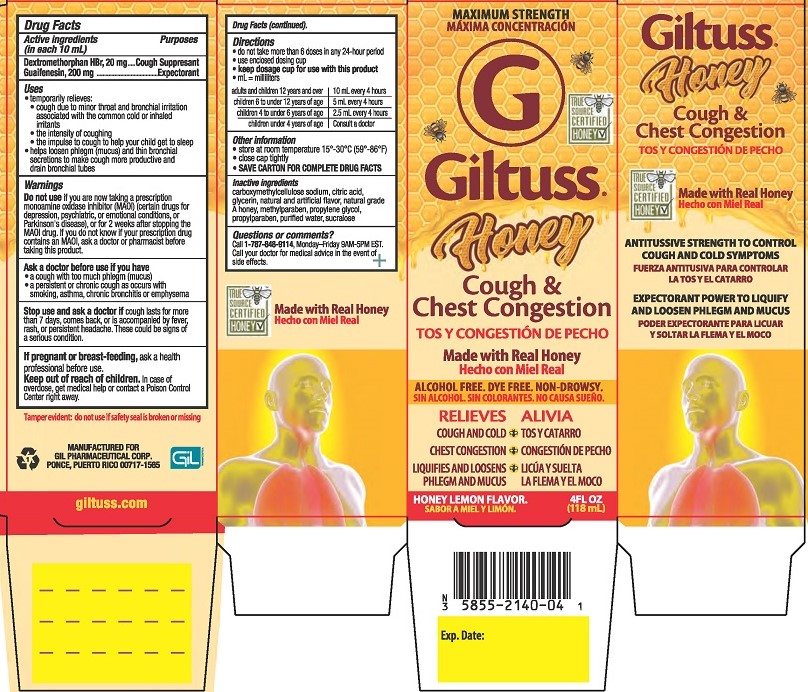 DRUG LABEL: Giltuss Honey Cough and Chest Congestion
NDC: 58552-140 | Form: SOLUTION
Manufacturer: Gil Pharmaceutical Corp
Category: otc | Type: HUMAN OTC DRUG LABEL
Date: 20251009

ACTIVE INGREDIENTS: GUAIFENESIN 200 mg/10 mL; DEXTROMETHORPHAN HYDROBROMIDE 20 mg/10 mL
INACTIVE INGREDIENTS: CARBOXYMETHYLCELLULOSE SODIUM; WATER; GLYCERIN; PROPYLENE GLYCOL; SUCRALOSE; ANHYDROUS CITRIC ACID; HONEY; METHYLPARABEN; PROPYLPARABEN

Giltuss Honey Cough & Chest Congestion

Drug Facts

Active ingredients (in each 10 mL)

Dextromethorphan HBr, 20 mg

Guaifenesin, 200 mg

Purposes

Cough Suppresant

Expectorant

Uses

- temporarily relieves:
- cough due to minor throat and bronchial irritation associated with the common cold or inhaled irritants
- the intensity of coughing
- the impulse to cough to help your child get to sleep
- helps loosen phlegm (mucus) and thin bronchial secretions to make coughs more productive and drain bronchial tubes

Warnings

DO NOT USE

Do not useif you are now taking a prescription monoamine oxidase inhibitor (MAOI) (certain drugs for depression, psychiatric, or emotional conditions, or Parkinson’s disease), or for 2 weeks after stopping the MAOI drug. If you do not know if your prescription drug contains an MAOI, ask a doctor or pharmacist before taking this product.

Ask a doctor before use if you have

- a cough with too much phlegm (mucus)
- a persistent or chronic cough as occurs with smoking, asthma, chronic bronchitis, or emphysema

Stop use and ask a doctor ifcough lasts for more than 7 days, comes back, or is accompanied by fever, rash or persistent headache. These could be signs of a serious condition.

PREGNANCY OR BREAST FEEDING

If pregnant or breast-feeding, ask a health professional before use.

Keep out of reach of children.In case of overdose, get medical help or contact a Poison Control Center right away.

Directions

- do not take more than 6 doses in any 24-hour period
- use enclosed dosinc cup
- keep dosage cup for use with this product
- ml = milliliters
  adults and children 12 years and over | 10 mL every 4 hours
  children 6 to under 12 years of age | 5 mL every 4 hours
  children 4 to under 6 years of age | 2.5 mL every 4 hours
  children under 4 years of age | Consult a doctor

Other information

- store at room temperature 15°-30°C (59°-86°F)
- close cap tightly
- SAVE CARTON FOR COMPLETE DRUG FACTS

INACTIVE INGREDIENT

Inactive ingredientscarboxymethycellulose sodium, citric acid, glycerin, natural and artificial flavor, natural grade A honey, methylparaben, propylene glycol, propylparaben, purified water, sucralose.

Questions or comments?Call 1-787-848-9114, Monday-Friday 9AM - 5PM EST. Call your doctor for medical advice in the event of side effects.

Tamper Evident: do not use if safety seal is broken or missing.

MANUFACTURED FOR

GIL PHARMACEUTICAL CORP.

PONCE, PUERTO RICO 00717-1565

giltuss.com

PACKAGE LABEL

MAXIMUM STRENGTH

Giltuss®

Honey Cough & Chest Congestion

Made with real honey

ALCOHOL FREE. DYE FREE. NON-DROWSY

RELIEVES

COUGH AND COLD

CHEST CONGESTION

LIQUIFIES AND LOOSENS PHLEGM AND MUCUS

HONEY LEMON FLAVOR

4FL OZ (118 mL)